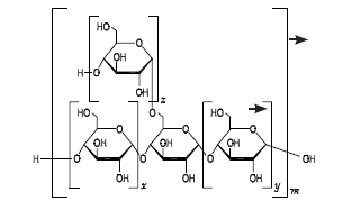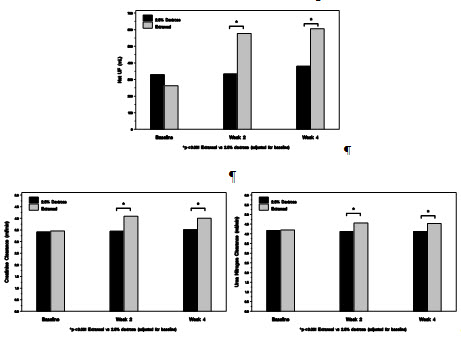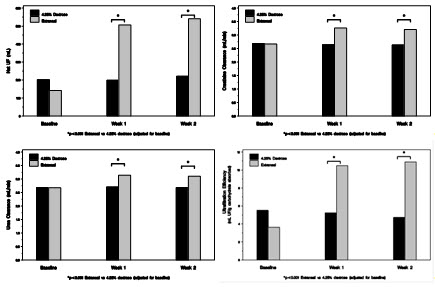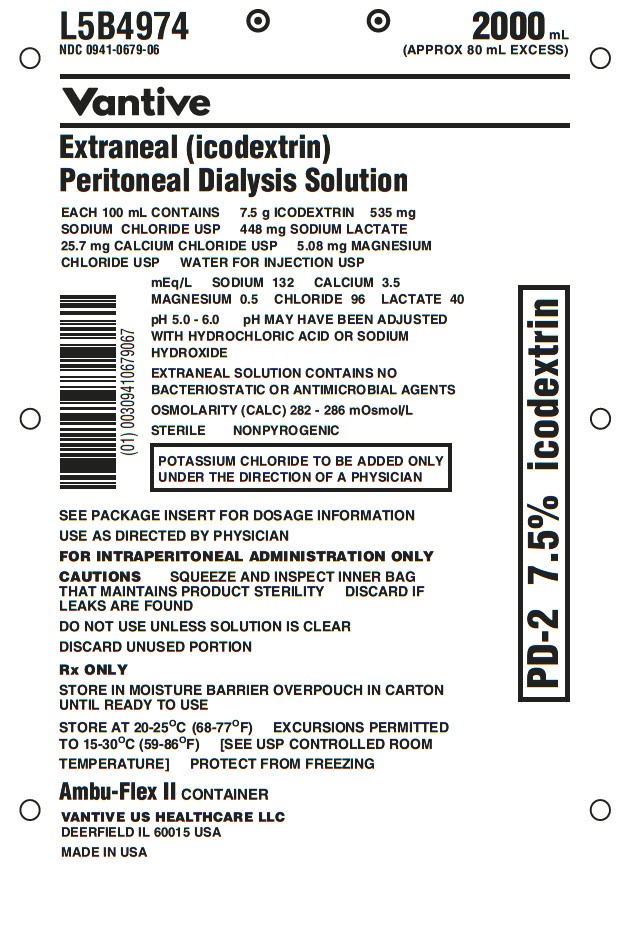 DRUG LABEL: EXTRANEAL
NDC: 0941-0679 | Form: INJECTION, SOLUTION
Manufacturer: Vantive US Healthcare LLC
Category: prescription | Type: HUMAN PRESCRIPTION DRUG LABEL
Date: 20250630

ACTIVE INGREDIENTS: ICODEXTRIN 7.5 g/100 mL; SODIUM CHLORIDE 535 mg/100 mL; SODIUM LACTATE 448 mg/100 mL; CALCIUM CHLORIDE 25.7 mg/100 mL; MAGNESIUM CHLORIDE 5.08 mg/100 mL
INACTIVE INGREDIENTS: WATER; HYDROCHLORIC ACID; SODIUM HYDROXIDE

HIGHLIGHTS OF PRESCRIBING INFORMATION

These highlights do not include all the information needed to use EXTRANEAL safely and effectively. See full prescribing information for EXTRANEAL.
EXTRANEAL (icodextrin) peritoneal dialysis solution
Initial U.S. Approval: 2002

1 INDICATIONS AND USAGE

- For a single daily exchange for the long (8- to 16- hour) dwell during continuous ambulatory peritoneal dialysis (CAPD) or automated peritoneal dialysis (APD) for the management of kidney failure in patients requiring long-term kidney replacement therapy. (1)
- To improve (compared to 4.25% dextrose) long-dwell ultrafiltration and clearance of creatinine and urea nitrogen in patients with high average or greater transport characteristics, as defined using the peritoneal equilibration test (PET). (1)

2 DOSAGE AND ADMINISTRATION

For intraperitoneal administration only. Not for intravenous or intra-arterial administration. Administer as a single daily peritoneal dialysis (PD) exchange for the long dwell. Dosage should be individualized by the prescribing physician experienced in the treatment of kidney failure in patients requiring long-term kidney replacement therapy with PD. (2.1)

3 DOSAGE FORMS AND STRENGTHS

7.5% icodextrin (75 grams icodextrin per 1000 milliliters) in an electrolyte solution containing 40 mEq/L lactate (3)

- 2 L and 2.5 L AMBU-FLEX II containers (APD)
- 2 L and 2.5 L ULTRABAG containers (CAPD)

4 CONTRAINDICATIONS

- Known hypersensitivity to icodextrin
- Maltose or isomaltose intolerance
- Glycogen storage disease
- Pre-existing severe lactic acidosis

5 WARNINGS AND PRECAUTIONS

- Use glucose-specific glucose monitoring systems when measuring blood glucose (5.1)
- Encapsulating peritoneal sclerosis (5.2)
- Peritonitis: Initiate appropriate antimicrobial therapy. (5.2)
- Hypersensitivity reactions: Serious reactions have been reported. Discontinue use of EXTRANEAL if serious reaction is suspected. (5.3)
- Monitor for lactic acidosis in patients at risk (5.4)
- Monitor for electrolyte, fluid, and nutrition imbalances (5.6)

6 ADVERSE REACTIONS

The most common adverse reaction (incidence > 5%) was rash. (6.1)

To report SUSPECTED ADVERSE REACTIONS, contact Vantive US Healthcare LLC at 1-855-857-0003 or FDA at 1-800-FDA-1088 or www.fda.gov/medwatch.

FULL PRESCRIBING INFORMATION

1 INDICATIONS AND USAGE

EXTRANEAL (icodextrin) is indicated for a single daily exchange for the long (8- to 16- hour) dwell during continuous ambulatory peritoneal dialysis (CAPD) or automated peritoneal dialysis (APD) for the management of kidney failure in patients requiring long-term kidney replacement therapy. EXTRANEAL is also indicated to improve (compared to 4.25% dextrose) long-dwell ultrafiltration and clearance of creatinine and urea nitrogen in patients with high average or greater transport characteristics, as defined using the peritoneal equilibration test (PET) [see Clinical Pharmacology (12), Clinical Studies (14)].

2 DOSAGE AND ADMINISTRATION

2.1 Basic Dosing Information

EXTRANEAL is intended for intraperitoneal administration only. Not for intravenous or intra-arterial administration. Administer as a single daily exchange for the long dwell in continuous ambulatory peritoneal dialysis or automated peritoneal dialysis. The recommended dwell time is 8 to 16 hours. Administer over a period of 10 to 20 minutes at a rate that is comfortable for the patient.

The mode of therapy, frequency of treatment, exchange volume, duration of dwell, and length of dialysis should be initiated and supervised by the prescribing physician experienced in the treatment of kidney failure in patients requiring long-term kidney replacement therapy with peritoneal dialysis. It is recommended that patients being placed on peritoneal dialysis should be appropriately trained in a program that is under supervision of a physician.

2.2 Directions for Use

For complete CAPD and APD system preparation, see directions accompanying ancillary equipment.

Aseptic technique should be used throughout the peritoneal dialysis procedure.

For single-dose only.

Storage

Store in moisture barrier overwrap and in carton until ready to use [see How Supplied/Storage and Handling (16)].

Warming

For patient comfort, EXTRANEAL can be warmed to 37°C (98.6°F). Only dry heat should be used (e.g., heating pad, warming plate). Do not immerse EXTRANEAL in water for warming. Do not use a microwave oven to warm EXTRANEAL. Do not heat above 40°C (104°F).

To Open

To open, tear the overwrap down at the slit and remove the solution container. Some opacity of the plastic, due to moisture absorption during the sterilization process, may be observed. This does not affect the solution quality or safety and may often leave a slight amount of moisture within the overwrap.

Inspect for Container Integrity and Solution Appearance

Do not use EXTRANEAL if it is cloudy or discolored, if it contains particulate matter, or if the container is leaking.

Inspect the patient connector to ensure the pull ring is attached. Do not use if pull ring is not attached to the connector. Inspect the EXTRANEAL container for signs of leakage and check for minute leaks by squeezing the container firmly. If the container has frangible(s), inspect that they are positioned correctly and are not broken. Do not use EXTRANEAL if the frangible(s) are broken or leaks are suspected as sterility may be impaired.

For EXTRANEAL in ULTRABAG, inspect the tubing and drain container for presence of solution. Small droplets are acceptable, but if solution flows past the frangible prior to use, do not use and discard the units.

Adding Medications

The decision to add medication should be made by the physician after careful evaluation of the patient [see Drug Interactions (7), Clinical Pharmacology (12.3)].

If the re-sealable rubber plug on the medication port is missing or partly removed, do not use the product.

To add a medication:

1. Put on mask. Clean and/or disinfect hands.
2. Prepare medication port site using aseptic technique.
3. Using a syringe with a 1-inch long, 25- to 19-gauge needle, puncture the medication port and inject additive.
4. Reposition container with container ports up and evacuate medication port by squeezing and tapping it.
5. Mix solution and additive thoroughly.

Preparation for Administration

1. Put on mask. Clean and/or disinfect hands.
2. Place EXTRANEAL on work surface.
3. For ULTRABAG system for manual exchanges, uncoil tubing and drain bag. Ensure the patient transfer set is closed. Break the connector (Y-set) frangible.
4. Remove pull ring from connector of solution container. If continuous fluid flow from connector is observed, discard solution container. Once the pull ring has been removed, do not reuse the solution or container.
5. Immediately attach the solution container to patient connector (transfer set) or appropriate peritoneal dialysis set.
6. For AMBU-FLEX II, continue with therapy set-up as instructed in user manual or directions accompanying tubing sets for automated peritoneal dialysis.
7. For ULTRABAG, follow the below steps:
8. Clamp solution line and then break frangible near solution bag. Hang solution container and place the drainage container below the level of the abdomen.
9. Open transfer set to drain the solution from abdomen. If drainage cannot be established, contact your clinician. When drainage complete, close transfer set.
10. Remove clamp from solution line and flush new solution to flow into the drainage container for 5 seconds to prime the line. Clamp drain line after flush complete.
11. Open transfer set to fill. When fill complete, close transfer set and clamp solution line.
12. Put on mask. Clean and/or disinfect hands.
13. Disconnect ULTRABAG from transfer set and apply MINICAP.

Completion of Therapy

1. Following use, the drained fluid should be inspected for the presence of fibrin or cloudiness, which may indicate the presence of peritonitis.
2. Discard unused portion.

3 DOSAGE FORMS AND STRENGTHS

EXTRANEAL is a clear, colorless peritoneal dialysis solution containing icodextrin as the primary osmotic ingredient at a concentration of 7.5% (7.5 grams icodextrin per 100 milliliters) in an electrolyte solution with 40 mEq/L lactate.

EXTRANEAL is available in the following containers and fill volumes:

Container | Fill Volume | Peritoneal Dialysis Modality
ULTRABAG | 2 L, 2.5 L | CAPD
AMBU-FLEX II | 2 L, 2.5 L | APD

4 CONTRAINDICATIONS

EXTRANEAL is contraindicated in patients with:

- known hypersensitivity to icodextrin [see Warnings and Precautions (5.3)]
- maltose or isomaltose intolerance
- glycogen storage disease
- severe lactic acidosis, as EXTRANEAL contains lactate which may contribute to worsening acidosis if conversion to bicarbonate is impaired and may be associated with hyperventilation, lethargy, hypotension or irregular heart rhythms.

5 WARNINGS AND PRECAUTIONS

5.1 Unrecognized Hypoglycemia Resulting from Drug-Device Interaction

When measuring blood glucose levels in patients using EXTRANEAL (icodextrin) Peritoneal Dialysis Solution, do not use blood glucose monitoring devices using glucose dehydrogenase pyrroloquinolinequinone (GDH-PQQ)-, glucose-dye-oxidoreductase (GDO)-, and some glucose dehydrogenase flavin-adenine dinucleotide (GDH-FAD)-based methods because these systems may result in falsely elevated glucose readings (due to the presence of maltose). Falsely elevated glucose readings have led patients or health care providers to withhold treatment of hypoglycemia or to administer insulin inappropriately leading to unrecognized hypoglycemia. Falsely elevated glucose levels may be measured up to two weeks following cessation of EXTRANEAL (icodextrin) therapy when GDH-PQQ, GDO, and GDH-FAD-based blood glucose monitors and test strips are used.

Additionally, other glucose-measuring technologies, such as continuous glucose monitoring systems, may or may not be compatible with EXTRANEAL.

Always contact the device manufacturer for current information regarding compatibility and intended use of the device in the dialysis patient population. For additional information, please contact the Vantive Renal Clinical Help Line 1-888-RENAL-HELP or visit www.glucosesafety.com.

5.2 Peritonitis and Encapsulating Peritoneal Sclerosis

Infectious and aseptic peritonitis has been associated with EXTRANEAL use. Following EXTRANEAL use, inspect the drained fluid for the presence of fibrin or cloudiness, which may indicate the presence of peritonitis. Improper clamping or priming sequence may result in infusion of air into the peritoneal cavity, which may result in abdominal pain and/or peritonitis. If peritonitis occurs, treat with appropriate therapy.

Encapsulating peritoneal sclerosis (EPS), sometimes fatal, is a complication of peritoneal dialysis therapy and has been reported in patients using EXTRANEAL.

5.3 Hypersensitivity Reactions

Serious hypersensitivity reactions to EXTRANEAL have been reported such as toxic epidermal necrolysis, angioedema, serum sickness, erythema multiforme and vasculitis [see Adverse Reactions (6.1,6.2)]. Anaphylactic or anaphylactoid reactions may occur. Stop the infusion immediately and drain the solution from the peritoneal cavity if any signs or symptoms of a suspected hypersensitivity reaction develop [see Contraindications (4)]. Institute appropriate therapeutic countermeasures as clinically indicated.

5.4 Lactic Acidosis

Monitor patients with conditions known to increase the risk of lactic acidosis [e.g., severe hypotension or sepsis that can be associated with acute renal failure, inborn errors of metabolism, treatment with drugs such as nucleoside/nucleotide reverse transcriptase inhibitors (NRTIs)] for lactic acidosis before the start of treatment and during treatment with EXTRANEAL [see Contraindications (4)].

5.5 Overinfusion

Overinfusion of peritoneal dialysis solution volume into the peritoneal cavity may be characterized by abdominal distention, feeling of fullness and/or shortness of breath. Drain the peritoneal dialysis solution from the peritoneal cavity to treat overinfusion.

5.6 Electrolyte, Fluid, and Nutrition Imbalances

Peritoneal dialysis may affect a patient’s protein, water-soluble vitamin, potassium, sodium, chloride, bicarbonate, and magnesium levels and volume status [see Adverse Reactions (6)]. Monitor electrolytes and blood chemistry periodically and take appropriate clinical action.

Potassium is omitted from EXTRANEAL solutions because dialysis may be performed to correct hyperkalemia. In situations where there is a normal serum potassium level or hypokalemia, the addition of potassium chloride (up to a concentration of 4 mEq/L) may be indicated to prevent severe hypokalemia.

Monitor fluid status to avoid hyper- or hypovolemia and potentially severe consequences including congestive heart failure, volume depletion, and hypovolemic shock.

6 ADVERSE REACTIONS

6.1 Clinical Trials Experience

EXTRANEAL was originally studied in controlled clinical trials of 493 patients with kidney failure in patients requiring long-term kidney replacement therapy who received a single daily exchange of EXTRANEAL for the long dwell (8-to 16- hours). There were 215 patients exposed for at least 6 months and 155 patients exposed for at least one year. The population was 18-83 years of age, 56% male and 44% female, 73% Caucasian, 18% Black, 4% Asian, 3% Hispanic, and it included patients with the following comorbid conditions: 27% diabetes, 49% hypertension and 23% hypertensive nephropathy.

Because clinical trials are conducted under widely varying conditions, adverse reaction rates observed in clinical trials of a drug cannot be compared to rates in the clinical trials of another drug and may not reflect the rates observed in practice. The adverse reaction information from clinical trials does, however, provide a basis for identifying the adverse events that appear to be related to drug use and for approximating rates.

Rash was the most frequently occurring EXTRANEAL-related adverse reaction (5.5%, EXTRANEAL; 1.7% Control). Seven patients on EXTRANEAL discontinued treatment due to rash, and one patient on EXTRANEAL discontinued due to exfoliative dermatitis. The rash typically appeared within the first three weeks of treatment and resolved with treatment discontinuation or, in some patients, with continued treatment.

Table 1 shows the adverse events reported in these clinical studies regardless of causality, occurring in ≥ 5% of patients and more common on EXTRANEAL than control.

Table 1 - Adverse Experiences in ≥5% of Patients and More Common on EXTRANEAL
 | EXTRANEAL | Control
 | N = 493 | N = 347
Peritonitis | 26% | 25%
Upper respiratory infection | 15% | 13%
Hypertension | 13% | 8%
Rash | 10% | 5%
Headache | 9% | 7%
Abdominal Pain | 8% | 6%
Flu syndrome | 7% | 6%
Nausea | 7% | 5%
Cough increase | 7% | 4%
Edema | 6% | 5%
Accidental injury | 6% | 4%
Chest pain | 5% | 4%
Dyspepsia | 5% | 4%
Hyperglycemia | 5% | 4%

Clinical Laboratory Findings

An increase in mean serum alkaline phosphatase has been observed in clinical studies of ESRD patients receiving EXTRANEAL. No associated increases in other liver chemistry tests were observed. Serum alkaline phosphatase levels did not show progressive increase over a 12-month study period. Levels returned to normal approximately two weeks after discontinuation of EXTRANEAL.

Decreases in serum sodium and chloride have been observed in patients using EXTRANEAL. The mean change in serum sodium from baseline to the last study visit was -2.8 mmol/L for patients on EXTRANEAL and -0.3 mmol/L for patients on control solution. Four EXTRANEAL patients and two control patients developed serum sodium < 125 mmol/L. The mean change in serum chloride from baseline to last study visit was -2 mmol/L for EXTRANEAL patients and + 0.6 mmol/L for control patients. Similar changes in serum chemistries were observed in an additional clinical study in a subpopulation of high average/high transporter patients. The declines in serum sodium and chloride may be related to dilution resulting from the presence of icodextrin metabolites in plasma.

An apparent decrease in serum amylase activity has been observed in patients administered EXTRANEAL. Investigations indicate that icodextrin and its metabolites interfere with enzymatic-based amylase assays, resulting in inaccurately low values. This should be taken into account when evaluating serum amylase levels for diagnosis or monitoring of pancreatitis in patients using EXTRANEAL.

6.2 Post-Marketing Experience

The following adverse reactions have been identified during post-approval use of EXTRANEAL, or in conjunction with performing the peritoneal dialysis procedure. Because these reactions are reported voluntarily from a population of uncertain size, it is not possible to estimate their frequency reliably or to establish a causal relationship to drug exposure.

INFECTIONS AND INFESTATIONS: Fungal peritonitis, Peritonitis bacterial, Catheter related infection

BLOOD AND LYMPHATIC SYSTEM DISORDERS: Thrombocytopenia, Leukopenia, Leukocytosis

IMMUNE SYSTEM DISORDERS: Vasculitis, Serum sickness, Hypersensitivity

METABOLISM AND NUTRITION DISORDERS: Hypoglycemic shock, Dehydration

NERVOUS SYSTEM DISORDERS: Hypoglycemic coma, Burning sensation

EYE DISORDERS: Vision blurred

RESPIRATORY, THORACIC, AND MEDIASTINAL DISORDERS: Bronchospasm, Stridor

GASTROINTESTINAL DISORDERS: Encapsulating peritoneal sclerosis, Aseptic peritonitis, Ileus, Ascites, Inguinal hernia

SKIN AND SUBCUTANEOUS DISORDERS: Toxic epidermal necrolysis, Angioedema, Urticaria generalized, Prurigo, Dermatitis (including bullous, allergic and contact), Erythema, Onychomadesis, Dry skin, Skin chapped, Blister

MUSCULOSKELETAL, CONNECTIVE TISSUE DISORDERS: Musculoskeletal pain

REPRODUCTIVE SYSTEM AND BREAST DISORDERS: Penile edema, Scrotal edema

GENERAL DISORDERS AND ADMINISTRATIVE SITE CONDITIONS: Pyrexia, Chills, Malaise, Catheter site erythema, Catheter site inflammation, Infusion related reaction (including Infusion site pain, Instillation site pain)

INVESTIGATIONS: Liver function test abnormal, Urine output decreased

7 DRUG INTERACTIONS

As with other dialysis solutions, blood concentrations of dialyzable drugs may be reduced by dialysis. Dosage adjustment of concomitant medications may be necessary. In patients using cardiac glycosides (digoxin and others), plasma levels of calcium, potassium and magnesium must be carefully monitored [see Warnings and Precautions (5.6)].

Insulin: Patients with insulin-dependent diabetes may require modification of insulin dosage following initiation of treatment with EXTRANEAL. Monitor blood glucose and adjust insulin, if needed [see Warnings and Precautions (5.1)].

8 USE IN SPECIFIC POPULATIONS

8.1 Pregnancy

Risk Summary

EXTRANEAL is a pharmacologically inactive solution. While there are no adequate and well controlled studies in pregnant women, appropriate administration of EXTRANEAL with monitoring of hematology, blood chemistry, and fluid status is not expected to cause fetal harm.

The estimated background risk of major birth defects and miscarriage for the indicated population is unknown. All pregnancies have a background risk of birth defect, loss, or other adverse outcomes. In the U.S. general population, the estimated background risk of major birth defects and miscarriage in clinically recognized pregnancies is 2 to 4% and 15 to 20%, respectively.

8.2 Lactation

Risk Summary

It is not known whether icodextrin or its metabolites are excreted in human milk. The developmental and health benefits of breastfeeding should be considered along with the mother’s clinical need for EXTRANEAL and any potential adverse effects on the breastfed child from EXTRANEAL or from the mother’s underlying condition.

8.4 Pediatric Use

Safety and effectiveness in pediatric patients have not been established.

8.5 Geriatric Use

No formal studies were specifically carried out in the geriatric population. However, 140 of the patients in clinical studies of EXTRANEAL were age 65 or older, with 28 of the patients age 75 or older. No overall differences in safety or effectiveness were observed between these patients and patients under age 65. Although clinical experience has not identified differences in responses between the elderly and younger patients, greater sensitivity of some older individuals cannot be ruled out.

10 OVERDOSAGE

No clinical trial data are available on experiences of overdosage with EXTRANEAL. Overdosage of EXTRANEAL would be expected to result in higher levels of serum icodextrin and metabolites, but it is not known what signs or symptoms might be caused by exposure in excess of the exposures used in clinical trials. An increase in plasma osmolality or clinical manifestations of hypovolemia may occur. In the event of overdosage with EXTRANEAL, continued peritoneal dialysis with glucose-based solutions should be provided.

11 DESCRIPTION

EXTRANEAL (icodextrin) Peritoneal Dialysis Solution is a solution intended for intraperitoneal administration that contains the colloid osmotic agent icodextrin. Icodextrin is a cornstarch-derived, water-soluble glucose polymer linked by alpha (1-4) and less than 10% alpha (1-6) glucosidic bonds with a weight-average molecular weight between 13,000 and 19,000 Daltons and a number average molecular weight between 5,000 and 6,500 Daltons. The representative structural formula of icodextrin is:

Each 100 mL of EXTRANEAL contains:

Icodextrin | 7.5 g
Sodium Chloride, USP | 535 mg
Sodium Lactate | 448 mg
Calcium Chloride, USP | 25.7 mg
Magnesium Chloride, USP | 5.08 mg

Electrolyte content per liter:

Sodium | 132 mEq/L
Calcium | 3.5 mEq/L
Magnesium | 0.5 mEq/L
Chloride | 96 mEq/L
Lactate | 40 mEq/L

Water for Injection, USP qs

HCl/NaOH may have been used to adjust pH.

EXTRANEAL contains no bacteriostatic or antimicrobial agents.

Calculated osmolarity: 282-286 mOsm/L; pH=5.0-6.0

EXTRANEAL is a sterile, nonpyrogenic, clear solution packaged in AMBU-FLEX II and ULTRABAG containers. The container systems are composed of polyvinyl chloride.

Solutions in contact with the plastic container can leach out certain of its chemical components in very small amounts within the expiration period, e.g., di-2-ethylhexyl phthalate (DEHP), up to 5 parts per million; however, the safety of the plastic has been confirmed in tests in animals according to USP biological tests for plastic containers as well as by tissue culture toxicity studies.

12 CLINICAL PHARMACOLOGY

12.1 Mechanism of Action

EXTRANEAL is an isosmotic peritoneal dialysis solution containing glucose polymers (icodextrin) as the primary osmotic agent. Icodextrin functions as a colloid osmotic agent to achieve ultrafiltration during long peritoneal dialysis dwells. Icodextrin acts in the peritoneal cavity by exerting osmotic pressure across small intercellular pores resulting in transcapillary ultrafiltration throughout the dwell. Like other peritoneal dialysis solutions, EXTRANEAL also contains electrolytes to help normalize electrolyte balance and lactate to help normalize acid-base status.

12.2 Pharmacodynamics

EXTRANEAL results in a reduction in the absorbed caloric (carbohydrate) load compared to 4.25% hyperosmolar glucose solutions. Additionally, EXTRANEAL results in an increased ultrafiltration volume per gram of absorbed carbohydrate compared to hyperosmolar glucose solutions.

12.3 Pharmacokinetics

Absorption

Absorption of icodextrin from the peritoneal cavity follows zero-order kinetics consistent with convective transport via peritoneal lymphatic pathways. In a single-dose pharmacokinetic study using EXTRANEAL, a median of 40% (60 g) of the instilled icodextrin was absorbed from the peritoneal solution during a 12-hour dwell. Plasma levels of icodextrin rose during the dwell and declined after the dwell was drained. Peak plasma levels of icodextrin plus its metabolites (median Cpeak 2.2 g/L) were observed at the end of the long dwell exchange (median Tmax = 13 hours).

At steady-state, the mean plasma level of icodextrin plus its metabolites was about 5 g/L. In multi-dose studies, steady-state levels of icodextrin were achieved within one week. Plasma levels of icodextrin and metabolites return to baseline values within approximately two weeks following cessation of icodextrin administration.

Metabolism

Icodextrin is metabolized by alpha-amylase into oligosaccharides with a lower degree of polymerization (DP), including maltose (DP2), maltotriose (DP3), maltotetraose (DP4), and higher molecular weight species. In a single dose study, DP2, DP3 and DP4 showed a progressive rise in plasma concentrations with a profile similar to that for total icodextrin, with peak values reached by the end of the dwell and declining thereafter. Only very small increases in blood levels of larger polymers were observed. Steady-state plasma levels of icodextrin metabolites were achieved within one week and stable plasma levels were observed during long-term administration.

Some degree of metabolism of icodextrin occurs intraperitoneally with a progressive rise in the concentration of the smaller polymers in the dialysate during the 12-hour dwell.

Elimination

Icodextrin undergoes renal elimination in direct proportion to the level of residual renal function. Diffusion of the smaller icodextrin metabolites from plasma into the peritoneal cavity is also possible after systemic absorption and metabolism of icodextrin.

Special Populations

Geriatrics

The influence of age on the pharmacokinetics of icodextrin and its metabolites was not assessed.

Gender and Race

The influence of gender and race on the pharmacokinetics of icodextrin and its metabolites was not assessed.

Drug Interactions

Insulin

A clinical study in 6 insulin-dependent diabetic patients demonstrated no effect of EXTRANEAL on insulin absorption from the peritoneal cavity or on insulin’s ability to control blood glucose when insulin was administered intraperitoneally with EXTRANEAL. However, appropriate monitoring of blood glucose should be performed when initiating EXTRANEAL in diabetic patients and insulin dosage should be adjusted if needed [see Drug Interactions (7)].

Heparin

In vitro studies demonstrated no evidence of incompatibility of heparin with EXTRANEAL.

Antibiotics

Compatibility has been demonstrated with vancomycin, cefazolin, ceftazidime, gentamicin, and netilmicin. However, aminoglycosides should not be mixed with penicillins due to chemical incompatibility.

Minimum Inhibitory Concentration (MIC)

No formal clinical drug interaction studies have been performed. In vitro studies with EXTRANEAL and the following antibiotics have demonstrated no effects with regard to minimum inhibitory concentration (MIC): vancomycin, cefazolin, ampicillin, ampicillin/flucoxacillin, ceftazidime, gentamicin, and amphotericin.

13 NONCLINICAL TOXICOLOGY

13.1 Carcinogenesis, Mutagenesis, Impairment of Fertility

Icodextrin did not demonstrate evidence of genotoxicity potential in in vitro bacterial cell reverse mutation assay (Ames test); in vitro mammalian cell chromosomal aberration assay (CHO cell assay); and in the in vivo micronucleus assay in mice. Long-term animal studies to evaluate the carcinogenic potential of EXTRANEAL or icodextrin have not been conducted. Icodextrin is derived from maltodextrin, a common food ingredient.

A fertility study in rats where males and females were treated for four and two weeks, respectively, prior to mating and until day 17 of gestation at up to 1.5 g/kg/day (1/3 the human exposure on a mg/m^2 basis) revealed slightly low epididymal weights in parental males in the high dose group as compared to Control. Toxicological significance of this finding was not evident as no other reproductive organs were affected and all males were of proven fertility. The study demonstrated no effects of treatment with icodextrin on mating performance, fertility, litter response, embryo-fetal survival, or fetal growth and development.

14 CLINICAL STUDIES

14.1 Ultrafiltration, Urea and Creatinine Clearance

In the active-controlled trials of one to six months in duration, described below, EXTRANEAL used once-daily for the long dwell in either continuous ambulatory peritoneal dialysis (CAPD) or automated peritoneal dialysis (APD) therapy resulted in higher net ultrafiltration than 1.5% and 2.5% dextrose solutions, and higher creatinine and urea nitrogen clearances than 2.5% dextrose. Net ultrafiltration was similar to 4.25% dextrose across all patients in these studies. Effects were generally similar in CAPD and APD.

In an additional randomized, multicenter, active-controlled two-week study in high average/high transporter APD patients, EXTRANEAL used once daily for the long dwell produced higher net ultrafiltration compared to 4.25% dextrose. Mean creatinine and urea nitrogen clearances were also greater with EXTRANEAL and ultrafiltration efficiency was improved.

In 175 CAPD patients randomized to EXTRANEAL (N=90) or 2.5% dextrose solution (N=85) for the 8-15 hour overnight dwell for one month, mean net ultrafiltration for the overnight dwell was significantly greater in the EXTRANEAL group at weeks 2 and 4 (Figure 1). Mean creatinine and urea nitrogen clearances were also greater with EXTRANEAL (Figure 1).

Figure 1 - Mean Net Ultrafiltration, Mean Creatinine and Urea Nitrogen Clearance for the Overnight Dwell

In another study of 39 APD patients randomized to EXTRANEAL or 2.5% dextrose solution for the long, daytime dwell (10-17 hours) for three months, the net ultrafiltration reported during the treatment period was (mean ± SD) 278 ± 192 mL for the EXTRANEAL group and -138 ± 352 mL for the dextrose group (p<0.001). Mean creatinine and urea nitrogen clearances were significantly greater for EXTRANEAL than 2.5% dextrose at weeks 6 and 12 (p<0.001).

In a six-month study in CAPD patients comparing EXTRANEAL (n=28) with 4.25% dextrose (n=31), net ultrafiltration achieved during an 8-hour dwell averaged 510 mL for EXTRANEAL and 556 mL for 4.25% dextrose. For 12-hour dwells, net ultrafiltration averaged 575 mL for EXTRANEAL (n=29) and 476 mL for 4.25% dextrose (n=31). There was no significant difference between the two groups with respect to ultrafiltration.

In a two week study in high average/high transporter APD patients (4-hour D/P creatinine ratio >0.70 and a 4-hour D/D0 ratio <0.34, as defined by the peritoneal equilibration test (PET)), comparing EXTRANEAL (n=47) to 4.25% dextrose (n=45), after adjusting for baseline, the mean net ultrafiltration achieved during a 14 ± 2 hour dwell was significantly greater in the EXTRANEAL group than the 4.25% dextrose group at weeks 1 and 2 (p<0.001, see Figure 2). Consistent with increases in net ultrafiltration, there were also significantly greater creatinine and urea nitrogen clearances and ultrafiltration efficiency in the EXTRANEAL group (p<0.001, see Figure 2).

Figure 2 – Mean Net Ultrafiltration, Creatinine and Urea Nitrogen Clearances and Ultrafiltration Efficiency for the Long Dwell in High Average/High Transporter Patients

14.2 Peritoneal Membrane Transport Characteristics

After one year of treatment with EXTRANEAL during the long dwell exchange, there were no differences in membrane transport characteristics for urea and creatinine. The mass transfer area coefficients (MTAC) for urea, creatinine, and glucose at one year were not different in patients receiving treatment with EXTRANEAL or 2.5% dextrose solution for the long dwell.

16 HOW SUPPLIED/STORAGE AND HANDLING

EXTRANEAL (icodextrin) Peritoneal Dialysis Solution is available in the following containers and fill volumes:

Container | Fill Volume | NDC
ULTRABAG | 2 L | NDC 0941-0679-52
ULTRABAG | 2.5 L | NDC 0941-0679-53
AMBU-FLEX II | 2 L | NDC 0941-0679-06
AMBU-FLEX II | 2.5 L | NDC 0941-0679-05

Each 100 mL of EXTRANEAL contains 7.5 grams of icodextrin in an electrolyte solution with 40 mEq/L lactate.

Store at 20–25°C (68–77°F). Excursions permitted to 15–30°C (59–86°F) [See USP Controlled Room Temperature]. Protect from freezing.

Store in moisture barrier overwrap and in carton until ready to use.

17 PATIENT COUNSELING INFORMATION

Inform patients of the following:

- Only use glucose-specific glucose monitoring systems when measuring blood glucose. Falsely elevated blood glucose readings have led patients or health care providers to withhold treatment of hypoglycemia or to administer insulin inappropriately.
- Serious allergic reactions have been observed in patients using EXTRANEAL. Patients should call their doctor or get medical help if they experience any of these symptoms during treatment with EXTRANEAL: swelling of the face, eyes, lips, tongue, or mouth; trouble swallowing or breathing; skin rash, hives, sores in the mouth, on eyelids, or in the eyes; or, if skin blisters or peels.
- Peritonitis is a common side effect of patients on peritoneal dialysis. Symptoms of peritonitis may include cloudy peritoneal effluent, pain, erythema or drainage at the exit site, or fever.

Because patients self-administer EXTRANEAL at home, patients should also be instructed to:

- Follow the peritoneal dialysis (PD) training instructions given by the health care provider. Use aseptic technique throughout their entire PD procedure. Discard any unused EXTRANEAL solution [see Dosage and Administration (2.2)].
- Check the appearance of EXTRANEAL solution prior to use. Do not use EXTRANEAL if solution appears cloudy, discolored, contain visible particulate matter, or if there is evidence of leaking containers.
- Regularly check fluid balance and body weight to avoid over-hydration or dehydration and associated side effects.
- Inform their physicians about any changes in prescription or over-the-counter medications and supplements.
- Have periodic laboratory tests and routinely follow up with their health care provider.
- In case of damage, the container should be discarded.

Vantive, Ambu-Flex, Extraneal, MiniCap and UltraBag (or Ultrabag) are trademarks of Vantive Health LLC or its affiliates.

Vantive US Healthcare LLC
Deerfield, IL 60015 USA
Printed in USA

07-19-00-7294

PACKAGE LABEL - PRINCIPAL DISPLAY PANEL

Container Label

L5B4974
NDC 0941-0679-06

2000 mL
(APPROX 80 mL EXCESS)

Vantive

Extraneal (icodextrin)
Peritoneal Dialysis Solution

EACH 100 mL CONTAINS 7.5 g ICODEXTRN 535 mg
SODIUM CHLORIDE USP 448 mg SODIUM LACTATE
25.7 mg CALCIUM CHLORIDE USP 5.08 mg MAGNESIUM
CHLORIDE USP WATER FOR INJECTION USP

mEq/L SODIUM 132 CALCIUM 3.5
MAGNESIUM 0.5 CHLORIDE 96 LACTATE 40

pH 5.0 - 6.0 pH MAY HAVE BEEN ADJUSTED
WITH HYDROCHLORIC ACID OR SODIUM
HYDROXIDE

EXTRANEAL SOLUTION CONTAINS NO
BACTERIOSTATIC OR ANTIMICROBIAL AGENTS

OSMOLARITY (CALC) 282 - 286 mOsmol/L

STERILE NONPYROGENIC

POTASSIUM CHLORIDE TO BE ADDED ONLY
UNDER THE DIRECTION OF A PHYSICIAN

SEE PACKAGE INSERT FOR DOSAGE INFORMATION

USE AS DIRECTED BY A PHYSICIAN

FOR INTRAPERITONEAL ADMINISTRATION ONLY

CAUTIONS SQUEEZE AND INSPECT INNER BAG
THAT MAINTAINS PRODUCT STERILITY DISCARD IF
LEAKS ARE FOUND

DO NOT USE UNLESS SOLUTION IS CLEAR

DISCARD UNUSED PORTION

Rx ONLY

STORE IN MOISTURE BARRIER OVERPOUCH IN CARTON
UNTIL READY TO USE

STORE AT 20-25°C (68-77°F) EXCURSIONS PERMITTED
TO 15-30°C (59-86°F) [SEE USP CONTROLLED ROOM
TEMPERATURE] PROTECT FROM FREEZING

Ambu-Flex II CONTAINER

VANTIVE US HEALTHCARE LLC
DEERFIELD IL 60015 USA
MADE IN USA

Bar Code
(01) 00309410679067

PD-2 7.5% icodextrin